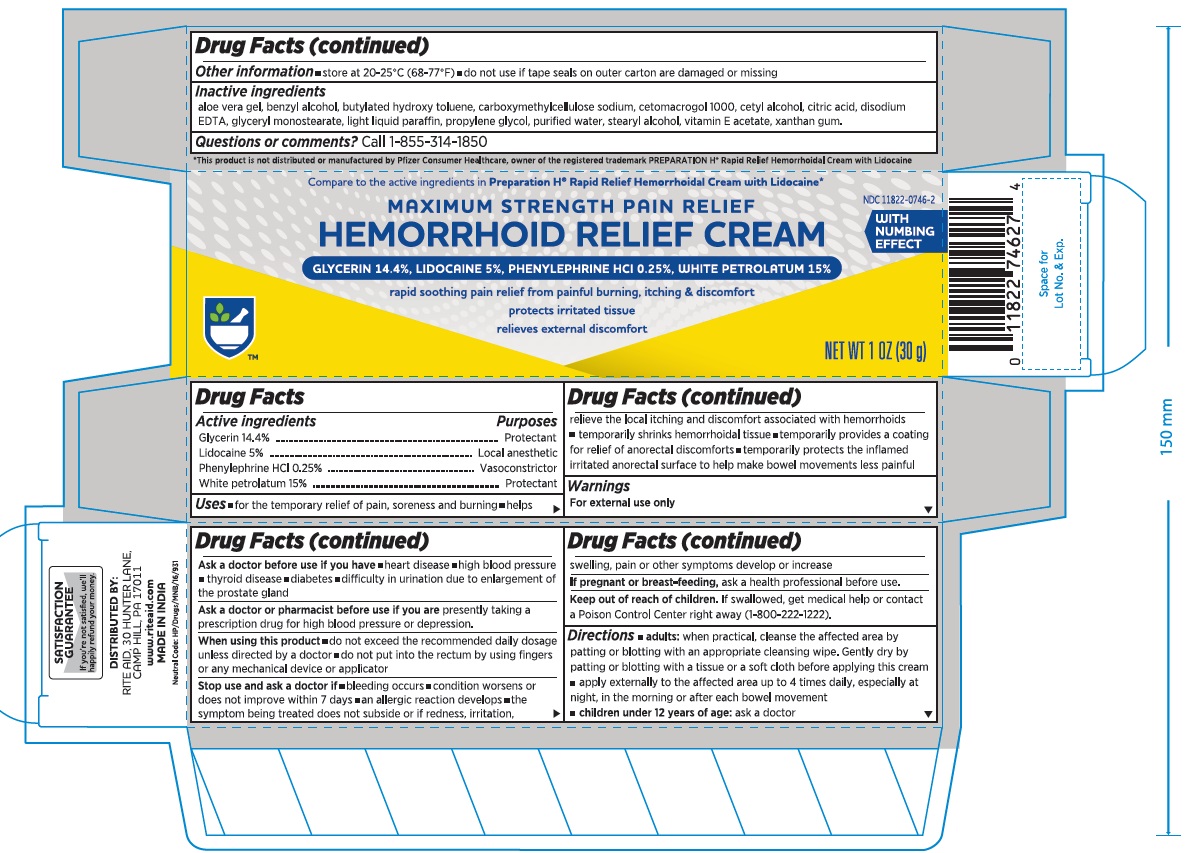 DRUG LABEL: Hemorrhoid Relief
NDC: 11822-0746 | Form: CREAM
Manufacturer: Rite Aid Hdgrts Corp
Category: otc | Type: HUMAN OTC DRUG LABEL
Date: 20201212

ACTIVE INGREDIENTS: PHENYLEPHRINE HYDROCHLORIDE 2.5 mg/1 g; PETROLATUM 150 mg/1 g; GLYCERIN 144 mg/1 g; LIDOCAINE 50 mg/1 g
INACTIVE INGREDIENTS: ALOE VERA LEAF; ANHYDROUS CITRIC ACID; BUTYLATED HYDROXYANISOLE; CARBOXYMETHYLCELLULOSE SODIUM, UNSPECIFIED FORM; CETYL ALCOHOL; CITRIC ACID MONOHYDRATE; EDETATE DISODIUM; GLYCERYL MONOSTEARATE; STEARYL ALCOHOL; PROPYLENE GLYCOL; LIGHT MINERAL OIL; WATER; .ALPHA.-TOCOPHEROL ACETATE; XANTHAN GUM

Hemorrhoid relief cream

Drug Facts

ACTIVE INGREDIENT

PURPOSE

Active ingredients | Purposes
Glycerin | Protectant
Lidocaine | Local anesthetic
Phenylephrine HCl | Vasoconstrictor
White Petrolatum | Protectant

Uses

- for temporary relief of pain, soreness and burning
- helps relieve the local itching and discomfort associated with hemorrhoids
- temporarily provides a coating for relief of anorectal discomforts
- temporarily protects the inflamed irritated anorectal surface to help make bowel movements less painful

Warnings

For external use only

When using this product

- do not exceed the recommended daily dosage unless directed by a doctor
- do not put into the rectum by using fingers or any mechanical device or applicator

Stop use and ask a doctor if

- rectal bleeding occurs
- condition worsens or does not improve within 7 days
- an allergic reaction develops
- the symptom being treated does not subside or if redness, irritation, swelling, pain, or other symptoms develop or increase

PREGNANCY OR BREAST FEEDING

If pregnant or breast-feeding, ask a health professional before use.

Keep out of reach of children. If swallowed, get medical help or contact a Poison Control Center right away.

Directions

- adults: when practical, cleanse the affected area by patting or blotting with an appropriate cleansing wipe. Gently dry by patting or blotting with a tissue or a soft cloth before applying this cream.
- apply externally to the affected area up to 4 times daily, especially at night, in the morning or after each bowel movement
- children under 12 years of age: ask a doctor

Other information

store at 20–25°C (68–77°F)

Inactive ingredients

aloe vera gel, benzyl alcohol, butylated hydroxy toluene, carboxymethylcellulose sodium, cetomacrogol 1000, cetyl alcohol, cetyl alcohol, citric acid, disodium EDTA, glyceryl monostearate, light liquid paraffin, propylene glycol, purified water, stearyl alcohol, Vitamin E, xanthan gum

Questions or comments?

Call 1-855-314-1850